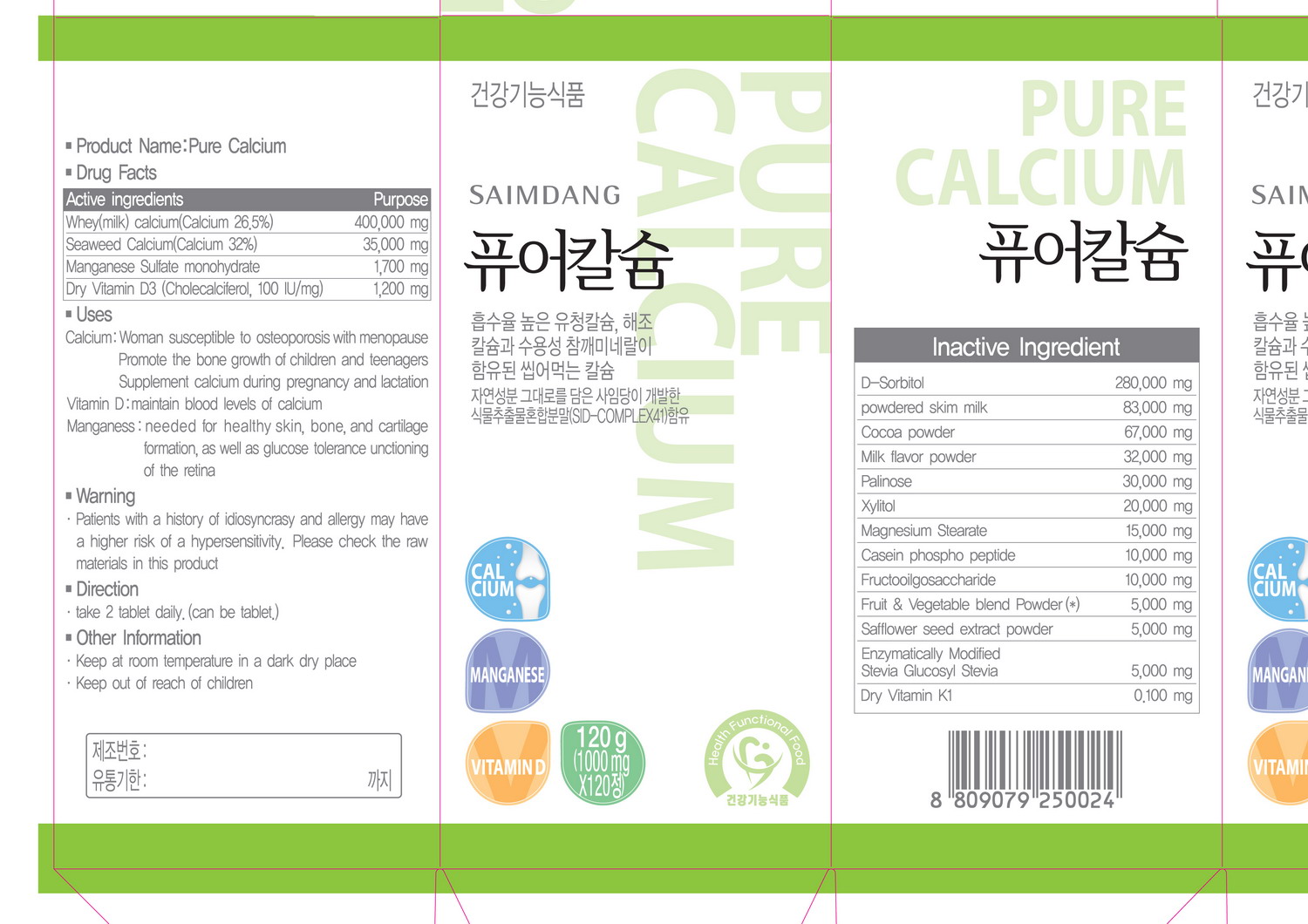 DRUG LABEL: Pure Calcium
NDC: 51220-3001 | Form: TABLET, CHEWABLE
Manufacturer: Saimdang Cosmetics Co., Ltd
Category: otc | Type: HUMAN OTC DRUG LABEL
Date: 20100821

ACTIVE INGREDIENTS: CALCIUM 435 mg/1 1; MANGANESE 1.7 mg/1 1; CHOLECALCIFEROL 1.2 mg/1 1

Drug Facts

Active ingredients: Calcium, Manganese, Vitamin D3

• Uses
Calcium: Woman susceptible to osteoporosis with menopause
Promote the bone growth of children and teenagers
Supplement calcium during pregnancy and lactation
Vitamin D: maintain blood levels of calcium
Manganese: needed for healthy skin, bone, and cartilage
formation, as well as glucose tolerance unconditioning
of the retina
• Warning
, Patients with a history of idiosyncrasy and allergy may have
a higher risk of a hypersensitivity, Please check the raw
materials in this product
• Direction
, take 2 tablet daily. (can be tablet.)
• Other Information
, Keep at room temperature in a dark dry place
. Keep out of reach of children

• Uses
Calcium: Woman susceptible to osteoporosis with menopause
Promote the bone growth of children and teenagers
Supplement calcium during pregnancy and lactation
Vitamin D: maintain blood levels of calcium
Manganese: needed for healthy skin, bone, and cartilage
formation, as well as glucose tolerance unconditioning
of the retina

• Other Information
, Keep at room temperature in a dark dry place
. Keep out of reach of children

INDICATIONS AND USAGE

• Direction
, take 2 tablet daily. (can be tablet.)

• Warning
, Patients with a history of idiosyncrasy and allergy may have
a higher risk of a hypersensitivity, Please check the raw
materials in this product

DOSAGE AND ADMINISTRATION

• Direction
, take 2 tablet daily. (can be tablet.)

INACTIVE INGREDIENT

Inactive ingredients: sorbitol, milk, cocoa, xylitol, magnesium, safflower, stevia, vitamin K1